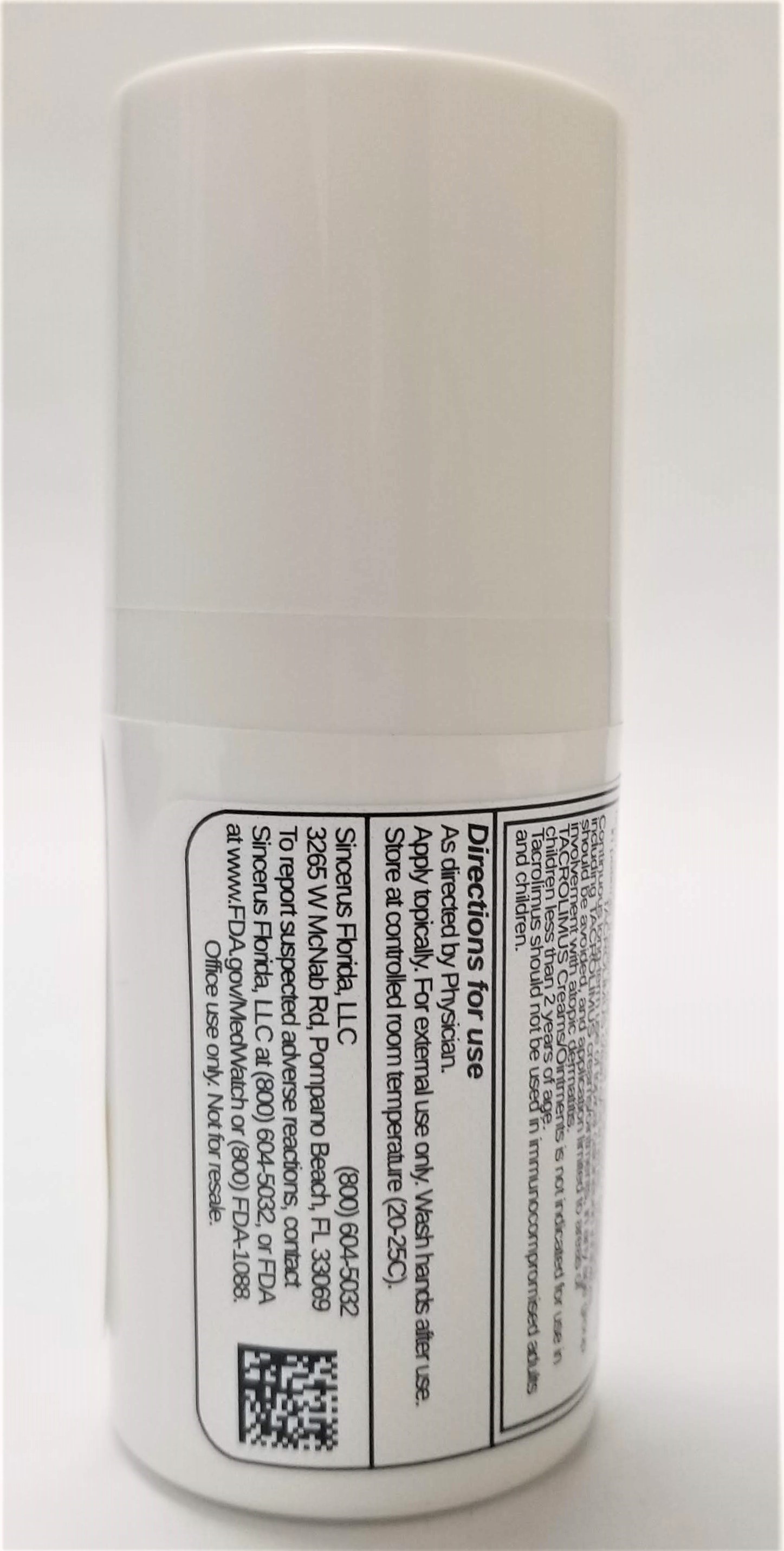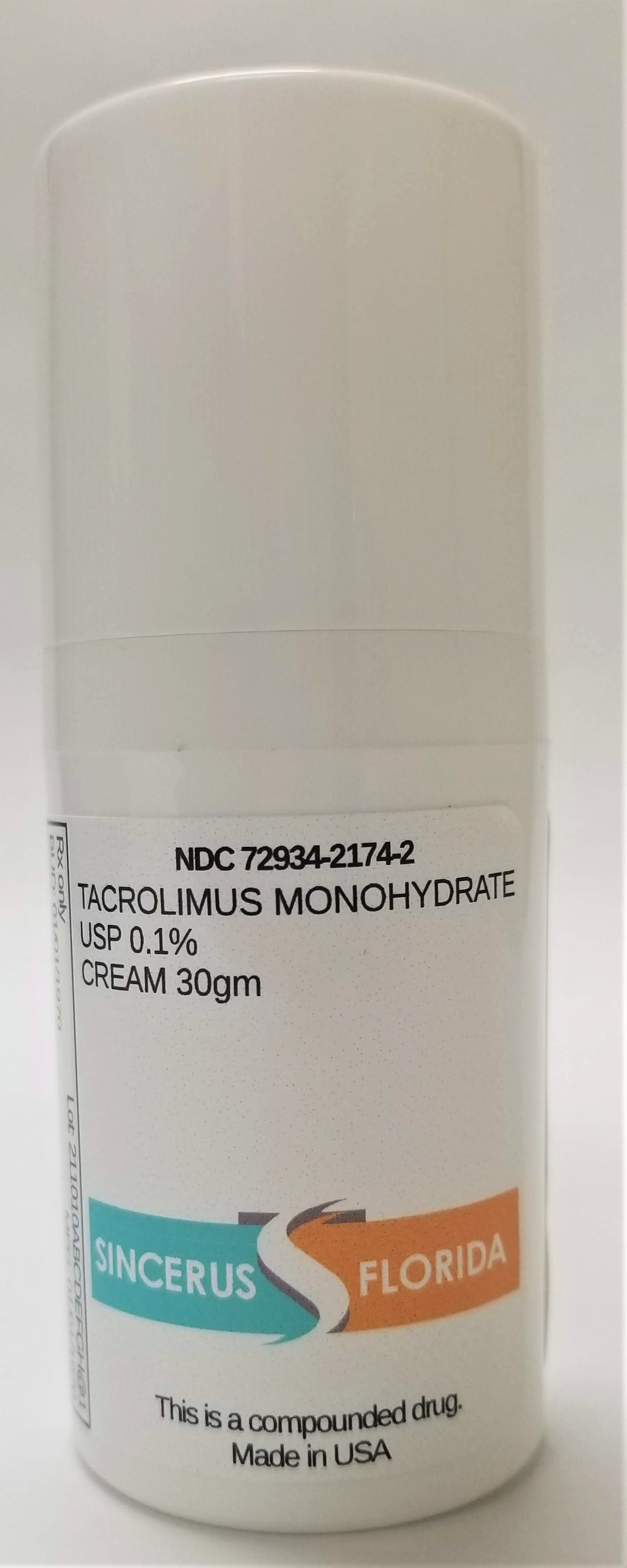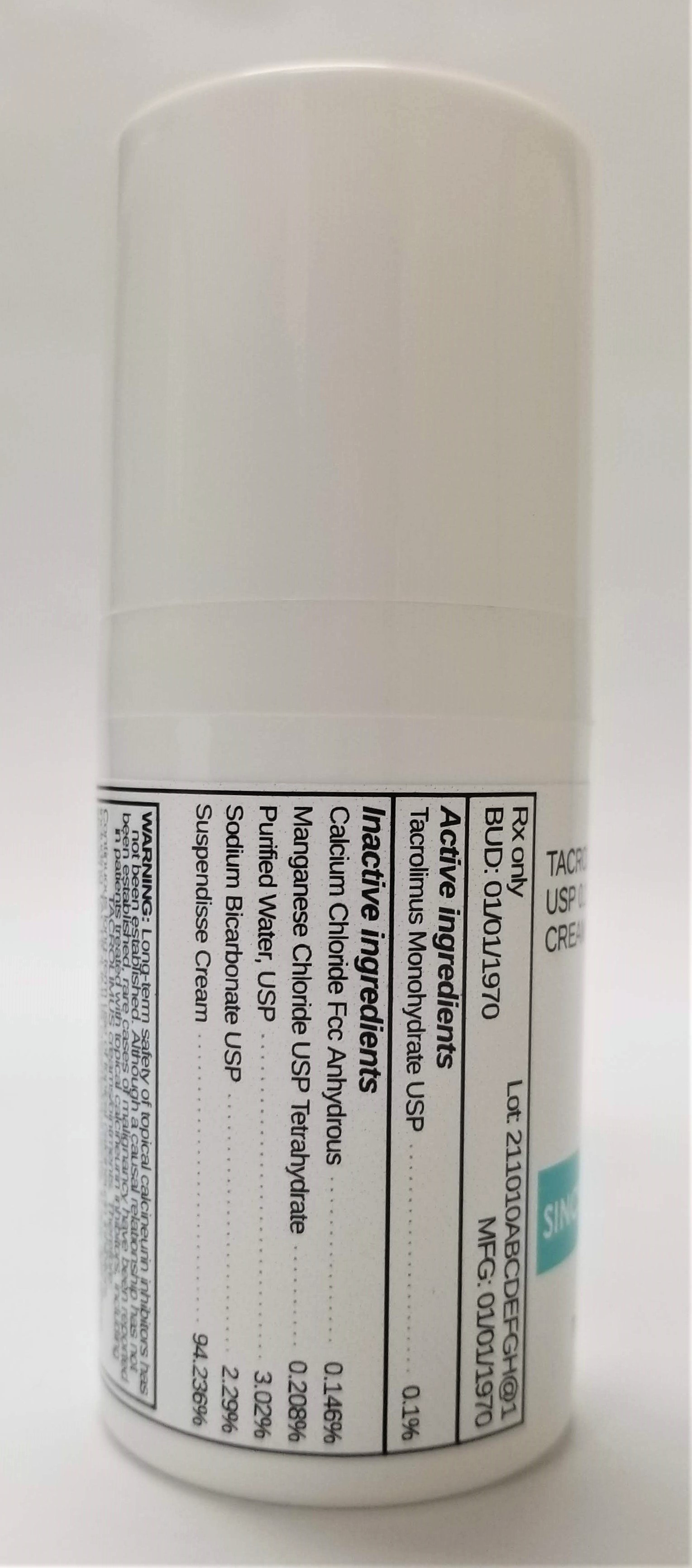 DRUG LABEL: TACROLIMUS 0.1% IN PSEUDOCATALASE
NDC: 72934-2174 | Form: CREAM
Manufacturer: Sincerus Florida, LLC
Category: prescription | Type: HUMAN PRESCRIPTION DRUG LABEL
Date: 20190424

ACTIVE INGREDIENTS: TACROLIMUS 0.1 g/100 g

TACROLIMUS 0.1% IN PSEUDOCATALASE